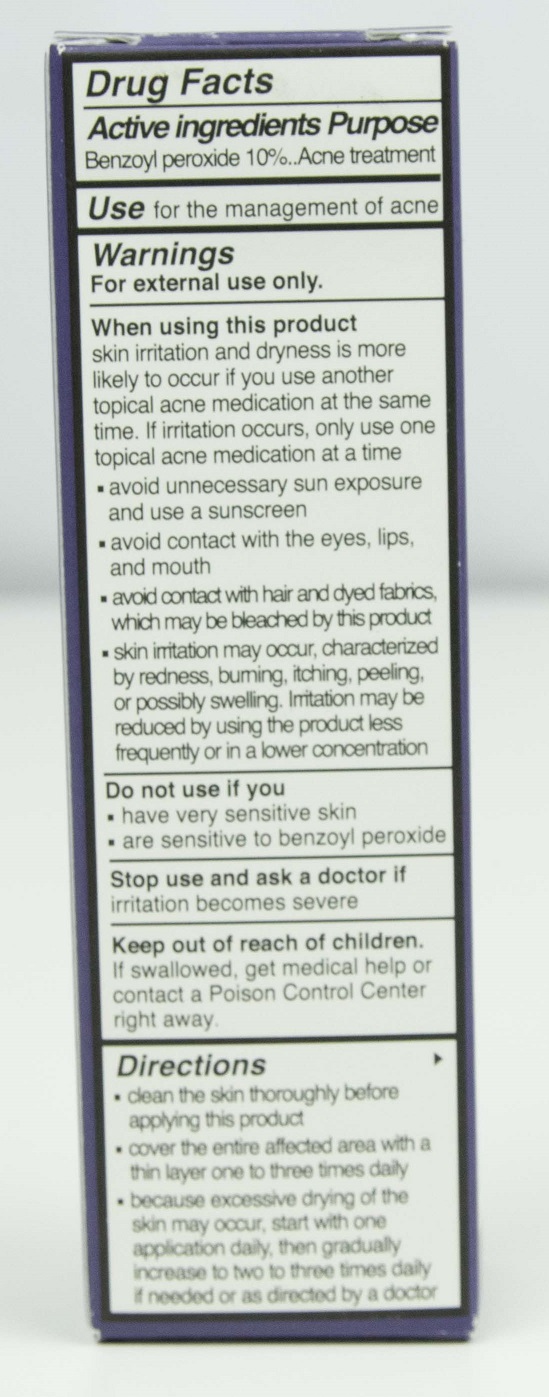 DRUG LABEL: SLMD Spot Treatment
NDC: 59958-401 | Form: GEL
Manufacturer: Owen Biosciences, Inc.
Category: otc | Type: HUMAN OTC DRUG LABEL
Date: 20250113

ACTIVE INGREDIENTS: BENZOYL PEROXIDE 10 g/100 g
INACTIVE INGREDIENTS: WATER 51.9 g/100 g; PROPANEDIOL 5 g/100 g; GLYCERIN 3 g/100 g; NEOPENTYL GLYCOL DIETHYLHEXANOATE 3 g/100 g

SLMD Moisturizer with SPF

Active Ingredients

Benzoyl Peroxide 10%

Use

for the management of acne

Warnings For external use only

When using this product

skin irritation and dryness is more likely to occur if you use another topical acne medication at the same time. If irritation occurs, only use one topical acne medication at a time.

- avoid unnecessary sun exposure and use a sunscreen
- avoid contact with the eyes, lips and mouth
- avoid contact with hair and dyed fabrics, which may be bleached by this product
- skin irritation may occur, characterized by redness, burning, itching, peeling, or possibly swelling. Irritation may be reduced by using this product less frequently or in a lower concentration

Keep out of reach of children.

If swallowed, get medical help or contact a Poison Control Center right away.

Directions

- Clean the skin thoroughly before applying product
- cover the entire affected area with a thin layer one to three times daily
- because excessive drying of the skin may occur, start with one application daily, then gradually increase to two to three times daily if needed or as directed by a doctor.

PURPOSE

acne treatment

DOSAGE AND ADMINISTRATION

topical cleanser

Inactive ingredients

Water (Aqua)
Propanediol
Glycerin
Neopentyl Glycol Diethylhexanoate
Dimethicone
Cyclopentasiloxane
Cyclohexasiloxane
Titanium Dioxide
C12-15 Alkyl Benzoate
Stearic Acid
Behenoxy Dimethicone
Behenyl Alcohol
Glyceryl Stearate
PEG-100 Stearate
Myristoyl Tetrapeptide-13
Acetyl Carboxymethyl Cocoyl Glycine
Panthenol
Tocopheryl Acetate
Sodium Hyaluronate
Allatoin
Glyceryl Oleate
Behenic Acid
Steareth-21
Steareth-2
Silica
Carbomer
Acrylates/C10-30 Alkyl Acrylate Crosspolymer
Phenoxyethanol
Ethylhexylglycerin
Fragrance
Tromethamine
Alumina
Polyhydroxystearic Acid

Do not use if

- have very senstive skin
- are sensitive to benzoyl peroxide

Stop us and ask a doctor if

irritation becomes severe

PACKAGE LABEL

Acne Spot Treatment Back.jpg